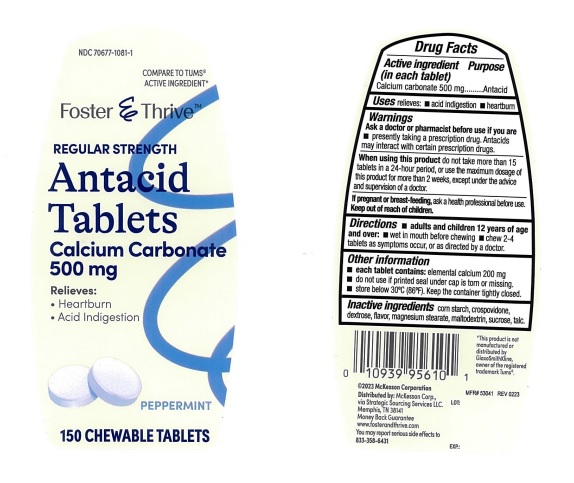 DRUG LABEL: Foster and Thrive Regular Strength Antacid Peppermint
NDC: 70677-1081 | Form: TABLET, CHEWABLE
Manufacturer: Strategic Sourcing Services LLC
Category: otc | Type: Human OTC Drug Label
Date: 20241212

ACTIVE INGREDIENTS: CALCIUM CARBONATE 500 mg/1 1
INACTIVE INGREDIENTS: STARCH, CORN; DEXTROSE, UNSPECIFIED FORM; MAGNESIUM STEARATE; MALTODEXTRIN; SUCROSE; TALC; CROSPOVIDONE, UNSPECIFIED

Foster and Thrive Extra Strength Antacid peppermint Chewable 113

ACTIVE INGREDIENT (in each tablet)

Calcium carbonate 500 mg

PURPOSE

Antacid

USES

relieves:

- acid indigestion
- heartburn

WARNINGS

.

ASK A DOCTOR OR PHARMACIST BEFORE USE IF YOU ARE

- presently taking a prescription drug. Antacids may interact with certain prescription drugs.

WHEN USING THIS PRODUCT

do not take more than 15 tablets in a 24-hour period, or use the maximum dosage of this product for more than 2 weeks, except under the advice and supervision of a doctor.

IF PREGNANT OR BREAST FEEDING,

ask a health professional before use.

KEEP OUT OF REACH OF CHILDREN

.

DIRECTIONS

- adults and children 12 years of age and over:
- Wet in mouth before chewing
- chew 2-4 tablets as symptoms occur, or as directed by a doctor.

OTHER INFORMATION

- each tablet contains: elemental calcium 200 mg
- do not use if printed seal under the cap is torn or missing.
- store below 30˚C (86˚F). keep the container tightly closed.

INACTIVE INGREDIENTS

corn starch, crospovidone, dextrose, flavor, magnesium stearate, maltodextrin, sucrose, talc.

PRINCIPAL DISPLAY PANEL

NDC 70677-1081-1
COMPARE TO TUMS® ACTIVE INGREDIENT*
Foster & Thrive TM REGULAR STRENGTHAntacid Tablets
Calcium Carbonate 500 mg
Relieves:

- Heartburn

- Acid Indigestion

PEPPERMINT

150 CHEWABLE TABLETS